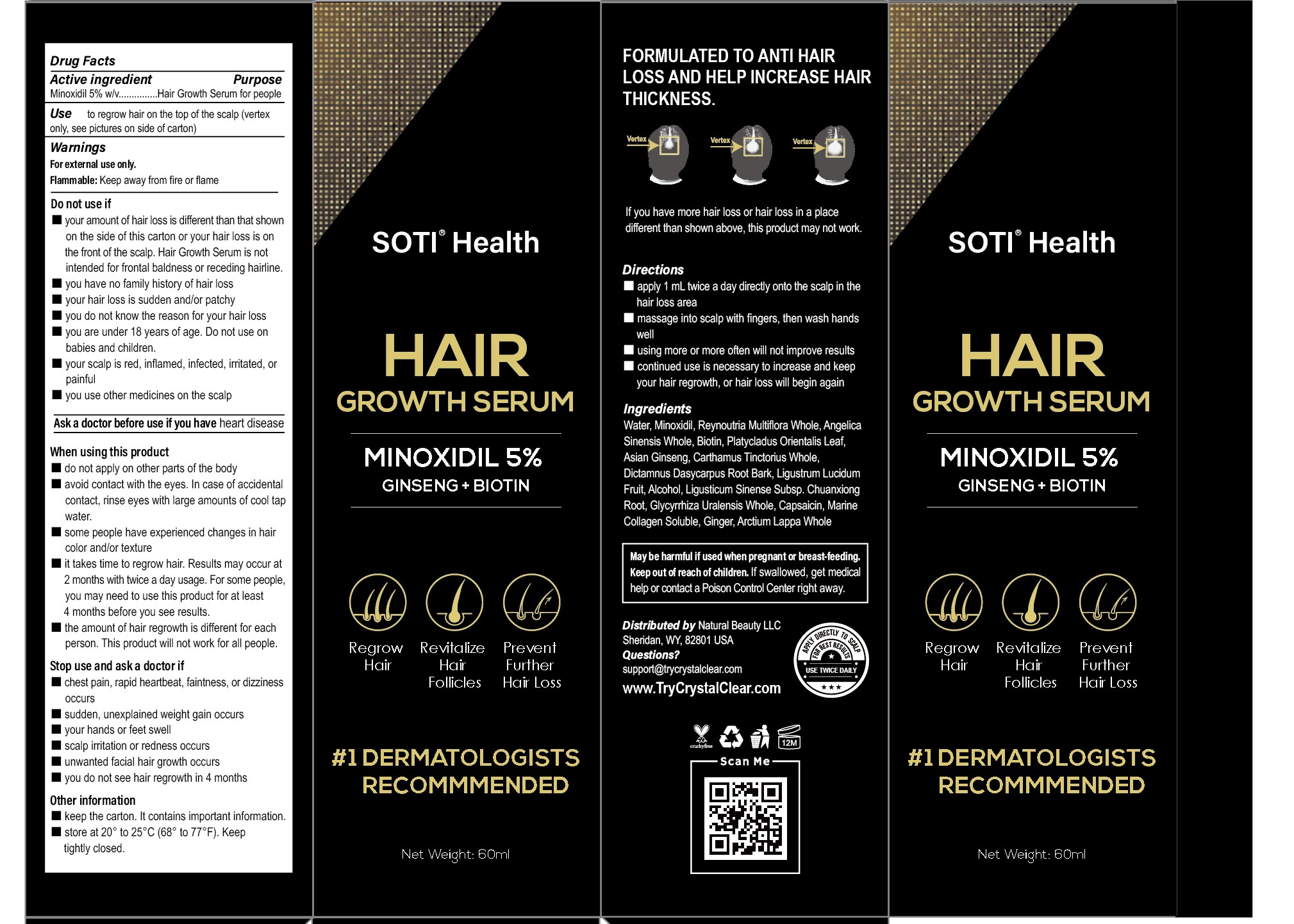 DRUG LABEL: SOTI HAIR GROWTH SERUM
NDC: 81653-013 | Form: LIQUID
Manufacturer: Guangzhou Jianyuan Biological Technology Co., Ltd.
Category: otc | Type: HUMAN OTC DRUG LABEL
Date: 20250116

ACTIVE INGREDIENTS: MINOXIDIL 5 g/100 mL
INACTIVE INGREDIENTS: ANGELICA SINENSIS WHOLE; PLATYCLADUS ORIENTALIS LEAF; LIGUSTRUM LUCIDUM FRUIT; GLYCYRRHIZA URALENSIS WHOLE; CAPSAICIN; DICTAMNUS DASYCARPUS ROOT BARK; ALCOHOL; ASIAN GINSENG; LIGUSTICUM SINENSE SUBSP. CHUANXIONG ROOT; BIOTIN; CARTHAMUS TINCTORIUS WHOLE; GINGER; ARCTIUM LAPPA WHOLE; WATER; REYNOUTRIA MULTIFLORA WHOLE; MARINE COLLAGEN, SOLUBLE

81653-013 Update

Active ingredient

Minoxidil 5% w/v

Use

to regrow hair on the top of the scalp (vertex only, see pictures on side of carton)

Purpose

Hair Growth Serum for people

Warnings

For external use only
Flammable: Keep away from fire or flame

Do not use if

■ our amount of hair loss is different than that shown the side of this carton or your hair loss is on the front of the scalp. Hair Growth Serum is not intended for frontal baldness or receding hairline

■ you have no family history of hair loss

■ your hair loss is sudden and/or patch

■ you do not know the reason for your hair loss

■ you are under 18 years of age. Do not use on babies and children

■ your scalp is red, inflamed, infected, irritated, or painful

■ you use other medicines on the scalp

Ask a doctor before use if you have

heart disease

When using this product

■ do not apply on other parts of the body

■ avoid contact with the eyes. In case of accidental contact, rinse eyes with large amounts of cool tap water

■ some people have experienced changes in hair color and or texture

■ it takes time to regrow hair. Results may occur at 2 months with twice a day usage. For some people, you may need to use this product for at least 4 months before you see results.

■ the amount of hair regrowth is different for each person. This product will not work for all people

Stop use and ask a doctor if

■ chest pain, rapid heartbeat, faintness, or dizziness occurs

■ sudden, unexplained weight gain occurs

■ your hands or feet swell

■ scalp irritation or redness occurs

■ unwanted facial hair growth occurs

■ you do not see hair regrowth in 4 months

Keep out of reach of children.

if swallowed, get medical help or contact a Poison Control Center right away.

Other information

keep the carton. t contains important information.
store at 20° to 25°C (68°to 77°F). Keep tightly closed.

Directions

■ Apply 1 ml twice a day directly onto the scalp in the hair loss area

■ massage into scalp with fingers, then wash hands well

■ using more or more often will not improve results

■ continued use is necessary to increase and keep your hair regrowth, or hair loss will begin again

Ingredients

Reynoutria Multiflora Whole

Angelica Sinensis Whole

Biotin

Platycladus Orientalis Leaf

Asian Ginseng

Carthamus Tinctorius Whole

Dictamnus Dasycarpus Root Bark

Ligustrum Lucidum Fruit

Alcohol

Ligusticum Sinense Subsp. Chuanxiong Root

Glycyrrhiza Uralensis Whole

Capsaicin

MARINE COLLAGEN SOLUBLE

Ginger

Arctium Lappa Whole